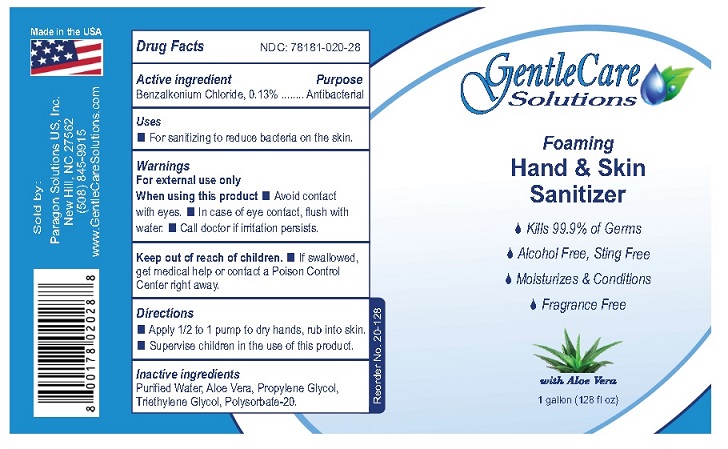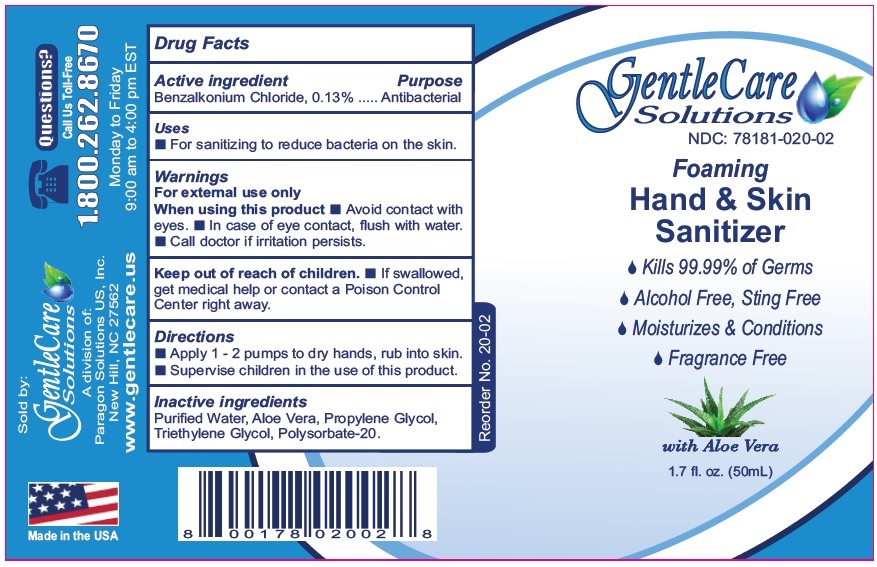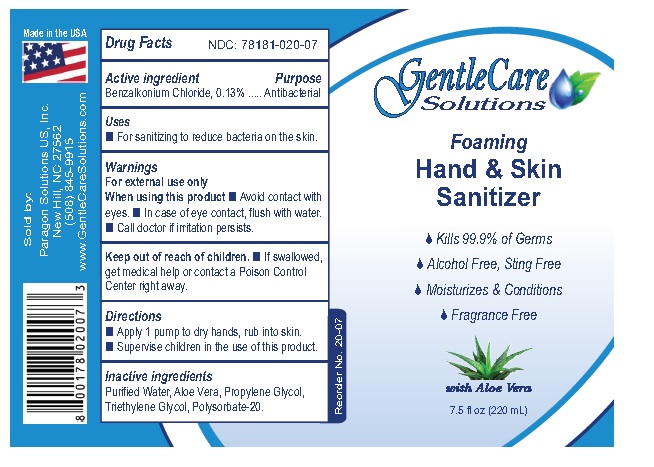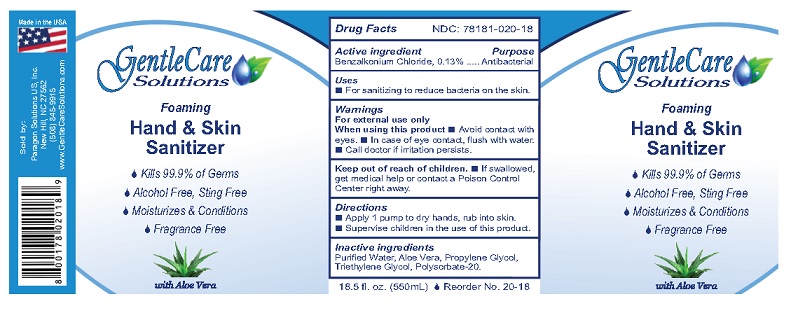 DRUG LABEL: GENTLECARE HAND AND SKIN SANITIZER
NDC: 78181-020 | Form: LIQUID
Manufacturer: PARAGON SOLUTIONS US, INC.
Category: otc | Type: HUMAN OTC DRUG LABEL
Date: 20251216

ACTIVE INGREDIENTS: BENZALKONIUM CHLORIDE 1.3 mg/1 mL
INACTIVE INGREDIENTS: WATER; ALOE VERA FLOWER; PROPYLENE GLYCOL; TRIETHYLENE GLYCOL; POLYSORBATE 20

Drug Facts

Active Ingredient

Benzalkonium Chloride, 0.13%

Purpose

Antibacterial

Uses
■ For sanitizing to reduce bacteria on the skin.

Warnings
For external use only
When using this product■ Avoid contact with
eyes. ■ In case of eye contact, flush with water.
■ Call doctor if irritation persists.

Keep out of reach of children. ■ If swallowed,
get medical help or contact a Poison Control
Center right away.

Directions
■ Apply 1 - 2 pump to dry hands, rub into skin.
■ Supervise children in the use of this product.

Inactive ingredients
Purified Water, Aloe Vera, Propylene Glycol,
Triethylene Glycol, Polysorbate-20.

Principal Display Panel

GentleCare

Solutions

Foaming

Hand & Skin
Sanitizer

- Kills 99.99% of Germs
- Moisturizes & Conditions
- Alcohol Free, Sting Free
- Fragrance Free

with Aloe Vera
1.7 fl. oz. (50 mL)

Sold by:

GentleCare
Solutions

A division of:
Paragon Solutions US, Inc.
New Hill, NC 27562

www.gentlecare.us

Questions?

Call Us Toll Free

1.800.262.8670
Monday to Friday
9:00 am to 4:00 pm EST

1.7 FL OZ

7.5 FL OZ

16.5 FL OZ

1 GAL

res